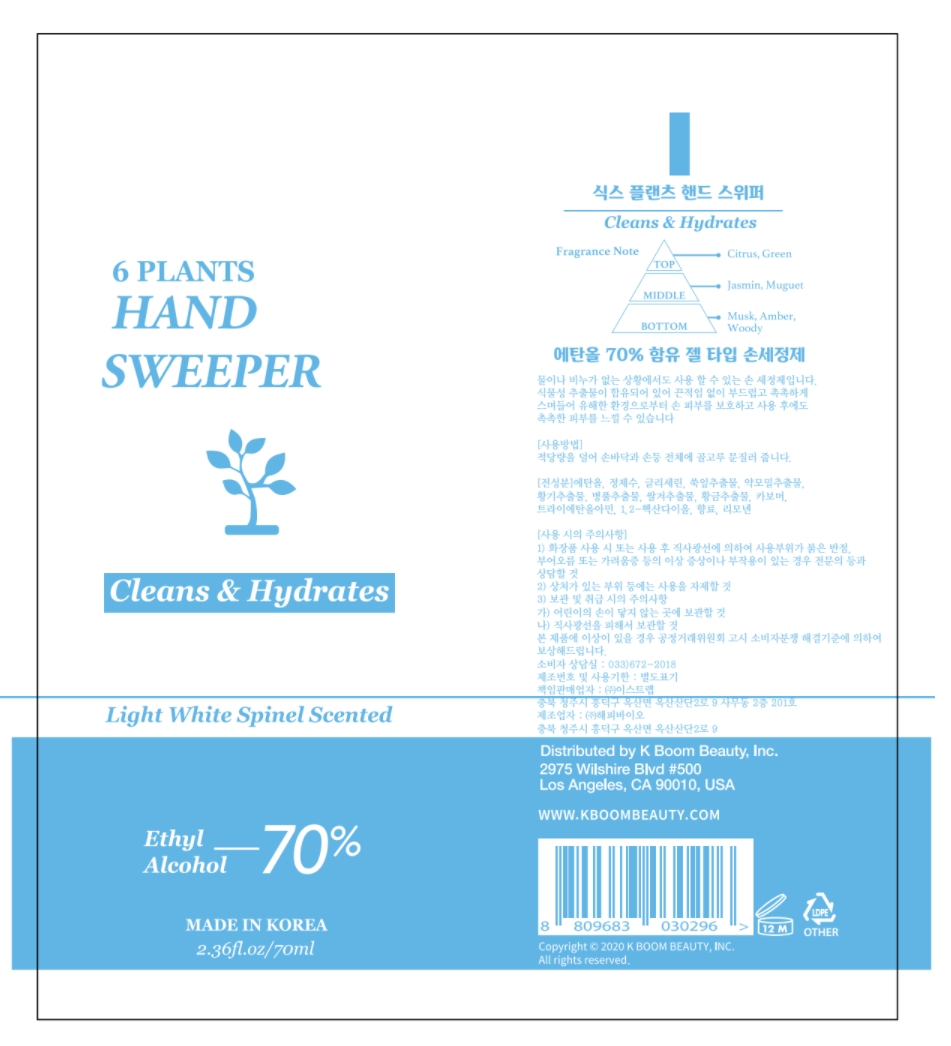 DRUG LABEL: 6 PLANTS HAND SWEEPER
NDC: 76656-101 | Form: GEL
Manufacturer: K BOOM BEAUTY INC
Category: otc | Type: HUMAN OTC DRUG LABEL
Date: 20200908

ACTIVE INGREDIENTS: ALCOHOL 70 mL/100 mL
INACTIVE INGREDIENTS: CENTELLA ASIATICA; HOUTTUYNIA CORDATA FLOWERING TOP; WATER; ARTEMISIA PRINCEPS LEAF; RICE BRAN; SCUTELLARIA BAICALENSIS ROOT; CARBOMER HOMOPOLYMER, UNSPECIFIED TYPE; 1,2-HEXANEDIOL; GLYCERIN

6 PLANTS HAND SWEEPER

Active ingredient

Alcohol (70%)

Purpose

Antiseptic

Uses

Hand Sanitizer to help reduce bacteria that potentially can cause disease. For use when soap and water are not available.

Warnings

For external use only. Flammable. Keep away from heat or flame

Do not use

· in children less than 2 months of age

· on open skin wounds

When using this product keep out of eyes, ears, and mouth. In case of contact with eyes, rinse eyes thoroughly with water.

Stop use and ask a doctor if irritation or rash occurs. These may be signs of a serious condition.

Keep out of reach of children

If swallowed, get medical help or contact a Poison Control Center right away.

Other information

- Store between 15-30°C (59-86°F)
- Avoid freezing and excessive heat above 40°C (104°F)

Inactive ingredients

Water, Glycerin, Artemisia Princeps Leaf Extract,Houttuynia Cordata Extract, Astragalus Membranaceus Extract, Centella Asiatica Extract, Oryza Sativa (Rice) Bran Extract, Scutellaria Baicalensis Root Extract, Carbomer, Triethanolamine, 1,2-Hexanediol, Fragrance

Directions

- Place enough product on hands to cover all surfaces. Rub hands together until dry.
- Supervise children under 6 years of age when using this product to avoid swallowing.